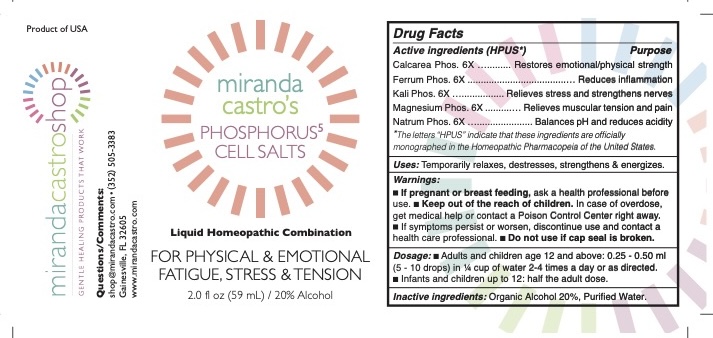 DRUG LABEL: Miranda Castros Phosphorus 5 Cell Salts
NDC: 82586-200 | Form: LIQUID
Manufacturer: MIRANDA CASTRO'S SHOP, LLC
Category: homeopathic | Type: HUMAN OTC DRUG LABEL
Date: 20251023

ACTIVE INGREDIENTS: TRIBASIC CALCIUM PHOSPHATE 6 [hp_X]/1 mL; SODIUM PHOSPHATE, DIBASIC, HEPTAHYDRATE 6 [hp_X]/1 mL; MAGNESIUM PHOSPHATE, DIBASIC TRIHYDRATE 6 [hp_X]/1 mL; POTASSIUM PHOSPHATE, DIBASIC 6 [hp_X]/1 mL; FERROSOFERRIC PHOSPHATE 6 [hp_X]/1 mL
INACTIVE INGREDIENTS: WATER; ALCOHOL

Miranda Castro's Phosphorus 5

Active Ingredients

Calcarea Phos. 6X

Ferrum Phos. 6X

Kali Phos. 6X

Magnesium Phos. 6X

Natrum Phos. 6X

Uses

Temporarily relaxes, destresses, strengthens & energizes.

Dosage

Adults and children 12 and above: 0.25 to 0.5 ml (5-10 drops) in ¼ cup of water 2-4 times a day or as directed.

Infants and children up to 12: half the adult dose.

Inactive Ingredients: Organic alcohol 20%, Purified water

PURPOSE

Calcarea Phos. - Restores emotional/phisical strength

Ferrum Phos. - Reduces inflammation

Kali Phos. - Relieves stress and strengthens nerves

Magnesium Phos. - Relieves muscular tension and pain

Natrum Phos. Balances pH and reduces acidity

Keep out of reach of children. In case of overdose, get medical help or contact a Poison Control Center right away.

Warnings

If symptoms persist or worsen, discontinue use and contact a healthcare professional.

Do not use if cap seal is broken.

Questions/Comments

shop@mirandacastro.com (352) 505-3383

If pregnant or breast-feeding, ask a health professional before use.